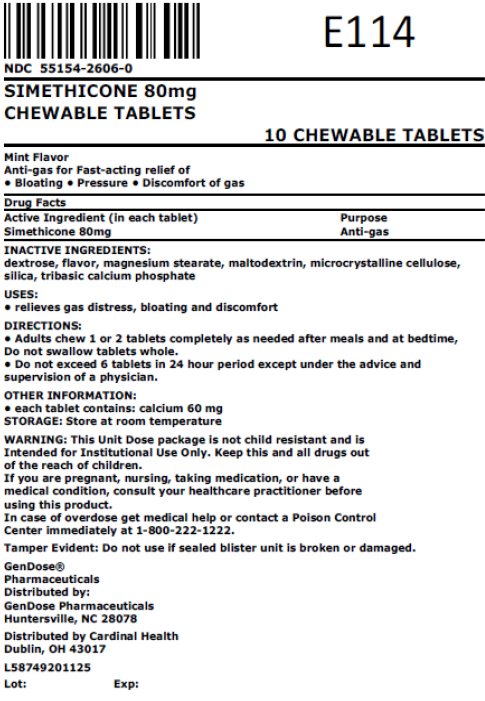 DRUG LABEL: SIMETHICONE 80MG
NDC: 55154-2606 | Form: TABLET, CHEWABLE
Manufacturer: Cardinal Health 107, LLC
Category: otc | Type: HUMAN OTC DRUG LABEL
Date: 20251218

ACTIVE INGREDIENTS: DIMETHICONE, UNSPECIFIED 80 mg/1 1
INACTIVE INGREDIENTS: DEXTROSE, UNSPECIFIED FORM; MAGNESIUM STEARATE; MALTODEXTRIN; MICROCRYSTALLINE CELLULOSE; SILICON DIOXIDE; TRIBASIC CALCIUM PHOSPHATE

SIMETHICONE 80 mg CHEWABLE TABLETS

ACTIVE INGREDIENT (IN EACH TABLET)

SIMETHICONE 80MG

PURPOSE

ANTI-GAS

USES

- RELIEVES GAS DISTRESS, BLOATING, AND DISCOMFORT

WARNINGS

- GET MEDICAL HELP OR CONTACT A POISON CONTROL CENTER IMMEDIATELY AT 1-800-222-1222.

KEEP OUT OF REACH OF CHILDREN.

DIRECTIONS

- ADULTS CHEW 1 OR 2 TABLETS COMPLETELY AS NEEDED AFTER MEALS AND AT BEDTIME. DO NOT SWALLOW TABLETS WHOLE.
- DO NOT EXCEED 6 TABLETS IN 24 HOUR PERIOD EXCEPT UNDER THE ADVICE AND SUPERVISION OF A PHYSICIAN.

OTHER INFORMATION

- EACH TABLET CONTAINS: CALCIUM 60MG
- STORE AT ROOM TEMPERATURE

INACTIVE INGREDIENTS

DEXTROSE, FLAVOR, MAGNESIUM STEARATE, MALTODEXTRIN, MICROCRYSTALLINE CELLULOSE, SILICA, TRIBASIC CALCIUM PHOSPHATE

.

Overbagged with 10 chewable tablets per bag, NDC 55154-2606-0

WARNING: This Unit Dose package is not child resistant and is Intended for Institutional Use Only. Keep this and all drugs out of the reach of children.

Distributed By:

Cardinal Health

Dublin, OH 43017

L58749201125

LB81210X09

Principal Display Panel

NDC 55154-2606-0

SIMETHICONE 80mg

CHEWABLE TABLETS

10 CHEWABLE TABLETS